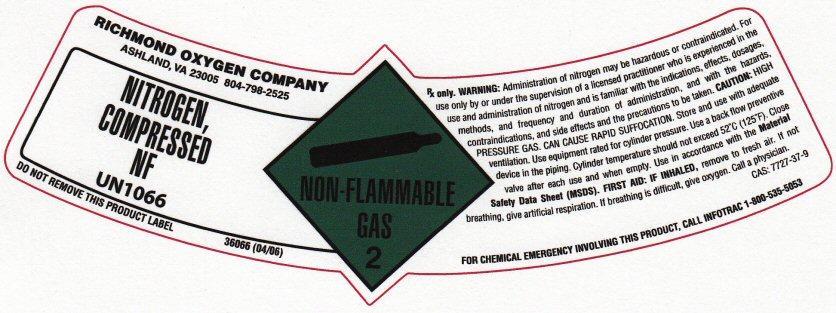 DRUG LABEL: NITROGEN
NDC: 59534-002 | Form: GAS
Manufacturer: Richmond Oxygen Company Inc.
Category: prescription | Type: HUMAN PRESCRIPTION DRUG LABEL
Date: 20241028

ACTIVE INGREDIENTS: NITROGEN 99 L/100 L

Nitrogen Label

RICHMOND OXYGEN COMPANY ASHLAND, VA 23005 804-798-2525

NITROGEN NF COMPRESSED UN 1066 NON-FLAMMABLE-2 DO NOT REMOVE THIS PRODUCT LABEL 36066 (04/06)
Rx ONLY. WARNING: ADMINISTRATION OF NITROGEN MAY BE HAZARDOUS OR CONTRAINDICATED. FOR USE ONLY BY OR UNDER THE SUPERVISION OF A LICENSED PRACTITIONER WHO IS EXPERIENCED IN THE USE AND ADMINISTRATION OF NITROGEN AND IS FAMILIAR WITH THE INDICATIONS, EFFECTS, DOSAGES, METHODS, AND FREQUENCY AND DURATION OF ADMINISTRATION, AND WITH THE HAZARDS, CONTRAINDICATIONS, AND SIDE EFFECTS AND THE PRECAUTIONS TO BE TAKEN
CAUTION; HIGH PRESSURE GAS. CAN CAUSE RAPID SUFFOCATION. STORE AND USE WITH ADEQUATE VENTILATION. USE EQUIPMENT RATED FOR CYLINDER PRESSURE. USE A BACK FLOW PREVENTIVE DEVISE IN THE PIPING. CYLINDER TEMPERATURE SHOULD NOT EXCEED 52 DEGREES C (125 DEGREES F) CLOSE VALVE AFTER EACH USE AND WHEN EMPTY. USE IN ACCORDANCE WITH THE MATERIAL SAFETY DATA SHEET (MSDS)

FIRST AID: IF INHALED, REMOVE TO FRESH AIR. IF NOT BREATHING, GIVE ARTIFICIAL RESPIRATION. IF BREATHING IS DIFFICULT, GIVE OXYGEN. CALL A PHYSICIAN.

CAS: 7727-37-9

FOR CHEMICAL EMERGENCY INVOLVING THIS PRODUCT, CALL INFOTRAC 1-800-535-5053